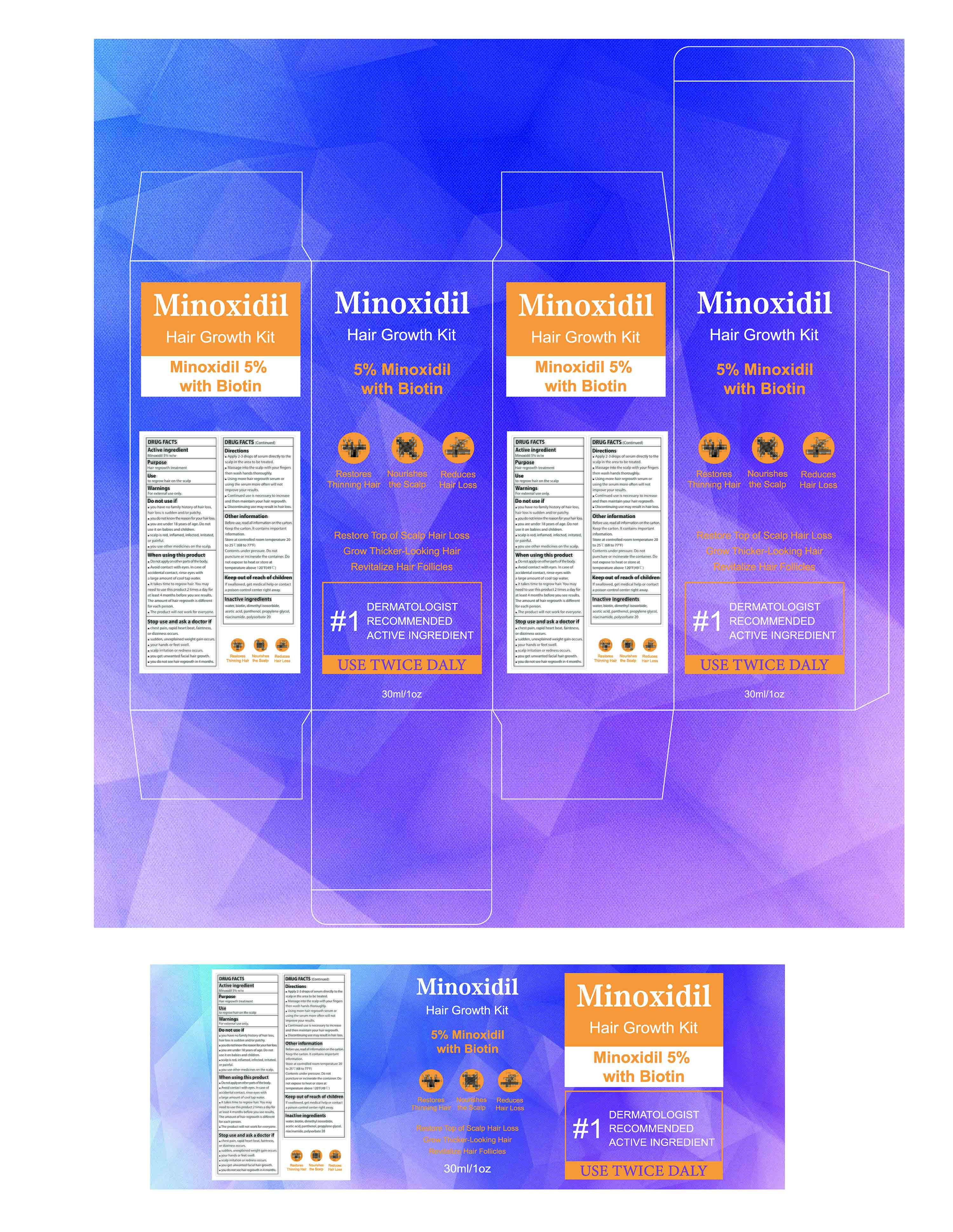 DRUG LABEL: 5% MINOXIDIL HAIR GROWTH SERUM liquid
NDC: 84735-012 | Form: LIQUID
Manufacturer: Hengyang Chuangjiujia Trading Co., Ltd.
Category: otc | Type: HUMAN OTC DRUG LABEL
Date: 20250619

ACTIVE INGREDIENTS: MINOXIDIL 5 g/100 mL
INACTIVE INGREDIENTS: BIOTIN; ACETIC ACID; PANTHENOL; DIMETHYL ISOSORBIDE; WATER; NIACINAMIDE; PROPYLENE GLYCOL; POLYSORBATE 20

84735-012 5% MINOXIDIL HAIR GROWTH SERUM liquid

ACTIVE INGREDIENT

Minoxidil 5%

PURPOSE

Hair regrowth treatment

INDICATIONS AND USAGE

to regrow hair on the scalp

WARNINGS

For external use only.

DO NOT USE

you have no family history of hair loss,hair loss is sudden and/or patchy.
you do not know the reason for your hair loss.
you are under 18 years of age. Do notuse it on babies and children.scalp is red, inflamed, infected, irritated,or painful.
you use other medicines on the scalp

WHEN USING

Do not apply on other parts ofthe body.
Avoid contact with eyes. in case ofaccidental contact, rinse eyes witha large amount of cool tap water.
lt takes time to regrow hair. You mayneed to use this product 2 times a day forat least 4 months before you see results The amount of hair regrowth is differentfor each person.
The product will not work for everyone.

STOP USE

chest pain, rapid heart beat, faintness,or dizziness occurs.
sudden, unexplained weight gain occurs.
your hands or feet swell.
scalp irritation or redness occurs.
you get unwanted facial hair growth.
you do not see hair regrowth in 4 months.

KEEP OUT OF REACH OF CHILDREN

If swallowed, get medical help or contacta poison control center right away.

DOSAGE AND ADMINISTRATION

Apply 2-3 drops of serum directly to thescalp in the area to be treated.
Massage into the scalp with your fingersthen wash hands thoroughly.
Using more hair regrowth serum orusing the serum more often will notimprove your results.
Continued use is necessary to increaseand then maintain your hair regrowth.
Discontinuing use may result in hair loss.

INACTIVE INGREDIENT

Water
Biotin
Dimethyl isosorbide
Acetic acid
Panthenol
Propylene glycol
Niacinamide
Polysorbate 20